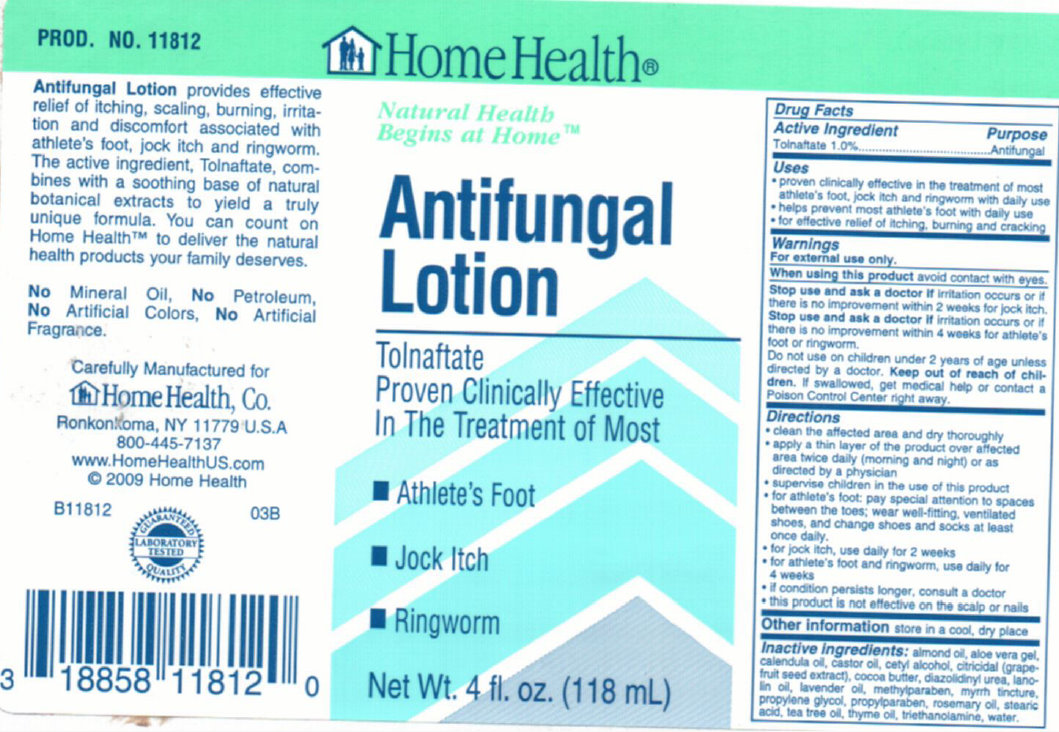 DRUG LABEL: HomeHealth Antifungal
NDC: 76020-100 | Form: LOTION
Manufacturer: Home Health
Category: otc | Type: HUMAN OTC DRUG LABEL
Date: 20231105

ACTIVE INGREDIENTS: TOLNAFTATE 10 mg/1 mL
INACTIVE INGREDIENTS: ALMOND OIL; ALOE VERA LEAF; CALENDULA OFFICINALIS FLOWER; CASTOR OIL; CETYL ALCOHOL; GRAPEFRUIT; COCOA BUTTER; DIAZOLIDINYL UREA; LANOLIN; LAVENDER OIL; METHYLPARABEN; PROPYLENE GLYCOL; PROPYLPARABEN; ROSEMARY OIL; STEARIC ACID; TEA TREE OIL; THYME OIL; TROLAMINE; WATER

HomeHealth Antifungal Lotion

Active Ingredient Purpose

Tolnaftate 1.0%..........................................................Antifungal

Uses

- proven clinically effective in the treatment of most athlete's foot, jock itch and ringworm with daily use. - helps prevent most athlete's foot with daily use. - for effective relief of itching, burning and cracking.

Warnings For external use only.

When using this product avoid contact with eyes.

Stop use and ask a doctor if irritation occurs or if there is no improvement within 2 weeks for jock itch. Stop use and ask a doctor if irritation occurs or if there is no improvement within 4 weeks for athlete's foot or ringworm.

Do not use on children under 2 years of age unless directed by a doctor.

Keep out of reach of children. If swallowed, get medical help or contact a Poison Control Center right away.

Directions

- clean the affected area and dry thoroughly; - apply a thin layer of the product over affected area twice daily (morning and night) or as directed by a physician; - supervise children in the use of this product; - for athlete's foot: pay special attention to spaces between the toes; wear well-fitting, ventilated shoes, and change shoes and socks at least once daily. - for jock itch, use daily for 2 weeks. - for athlete's foot and ringworm, use daily for 4 weeks. - if condition persists longer, consult a doctor. - this product is not effective on the scalp or nails.

Other information store in a cool, dry place.

INACTIVE INGREDIENT

Inactive Ingredients: Almond oil, aloe vera gel, calendula oil, castor oil, cetyl alcohol, citricidal (grapefruit seed extract), cocoa butter, diazolidinyl urea, lanolin oil, lavender oil, methylparaben, myrrh tincture, propylene glycol, propylparaben, rosemary oil, stearic acid, tea tree oil, thyme oil, triethanolamine, water.

DESCRIPTION

Antifungal Lotion provides effective relief of itching, scaling, burning, irritation and discomfort associated with athlete's foot, jock itch and ringworm. The active ingredient, Tolnaftate, combines with a soothing base of natural botanical extracts to yield a truly unique formula. You can count on Home Health to deliver the natural heath products your family deserves. No Mineral Oil, No petroleum, No Artificial Colors, No Artificial Fragrance. Carefully Manufactured for HomeHealth, Co. Ronkonxoma, NY 11779 U.S.A. 800-445-7137 www.HomeHealthUS.com 2009 Home Health B11812 03B

PACKAGE LABEL

HomeHealth Natural Health Begins at Home Antifungal Lotion Tolnaftate Proven Clinicallyl Effective In the Threatment of Most Athlete's Foot, Jock Itch, Ringworm Net Wt. 4 fl. oz. (118mL)